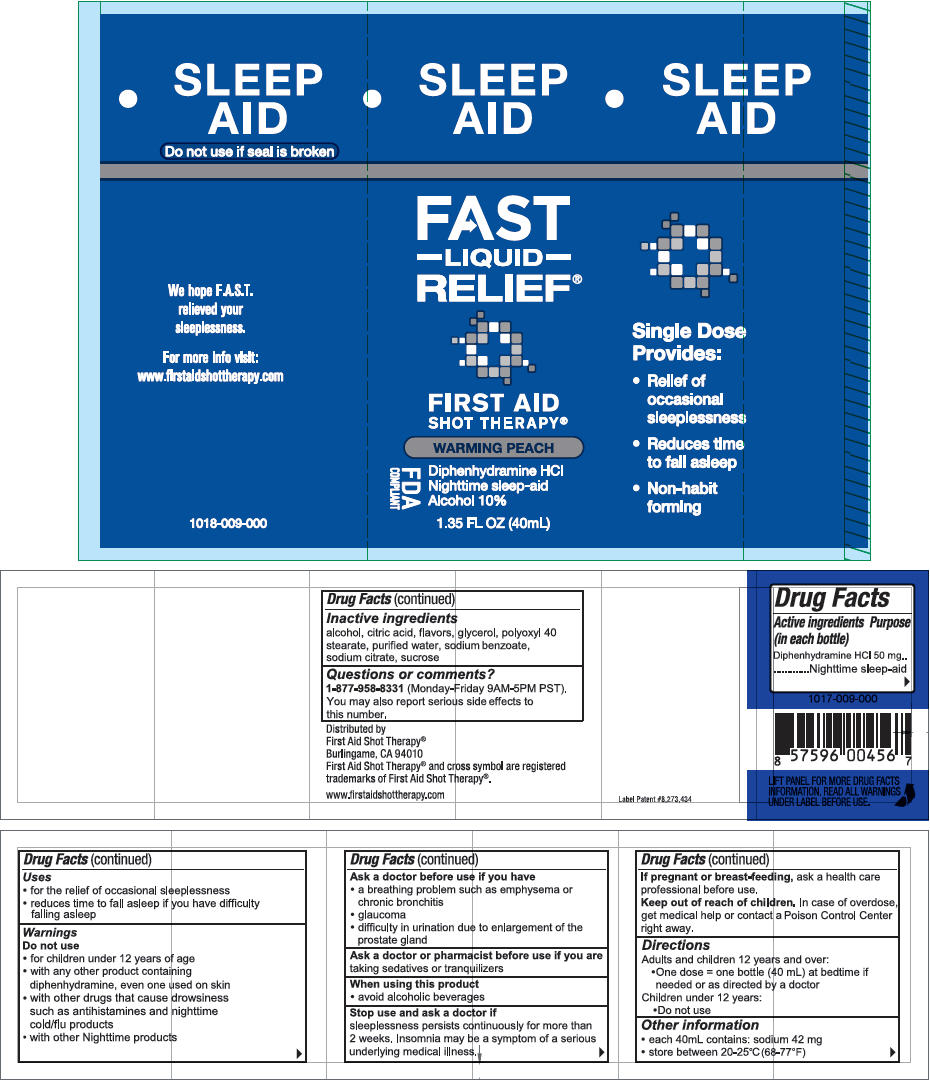 DRUG LABEL: First Aid Shot Therapy Sleep Aid
NDC: 57815-091 | Form: SOLUTION
Manufacturer: First Aid Beverages, Inc.
Category: otc | Type: HUMAN OTC DRUG LABEL
Date: 20160620

ACTIVE INGREDIENTS: Diphenhydramine Hydrochloride 50 mg/40 mL
INACTIVE INGREDIENTS: ALCOHOL; POLYOXYL 40 STEARATE; GLYCERIN; TRISODIUM CITRATE DIHYDRATE; ANHYDROUS CITRIC ACID; SODIUM BENZOATE; SUCROSE; WATER

First Aid Shot Therapy® Sleep Aid

Drug Facts

Active ingredients

Diphenhydramine HCl 50 mg

Purpose (in each bottle)

Nighttime sleep-aid

Uses

- for the relief of occasional sleeplessness
- reduces time to fall asleep if you have difficulty falling asleep

Warnings

Do not use

- for children under 12 years of age
- with any other product containing diphenhydramine, even one used on skin
- with other drugs that cause drowsiness such as antihistamines and nighttime cold/flu products
- with other Nighttime products

Ask a doctor before use if you have

- a breathing problem such as emphysema or chronic bronchitis
- glaucoma
- difficulty in urination due to enlargement of the prostate gland

Ask a doctor or pharmacist before use if you are taking sedatives or tranquilizers

When using this product

- avoid alcoholic beverages

Stop use and ask a doctor if

sleeplessness persists continuously for more than 2 weeks. Insomnia may be a symptom of a serious underlying medical illness.

PREGNANCY OR BREAST FEEDING

If pregnant or breast-feeding, ask a health care professional before use.

Keep out of reach of children. In case of overdose, get medical help or contact a Poison Control Center right away.

Directions

Adults and children 12 years and over:

- One dose = one bottle (40 mL) at bedtime if needed or as directed by a doctor

Children under 12 years:

- Do not use

Other information

- each 40mL contains: sodium 42 mg
- store between 20-25C°(68-77°F)

Inactive ingredients

alcohol, citric acid, flavors, glycerol, polyoxyl 40 stearate, purified water, sodium benzoate, sodium citrate, sucrose

Questions or comments?

1-877-958-8331 (Monday-Friday 9AM-5PM PST). You may also report serious side effects to this number.

Distributed by
First Aid Shot Therapy®
Burlingame, CA 94010

PRINCIPAL DISPLAY PANEL - 40 mL Bottle Label

SLEEP
AID

FAST
–LIQUID–
RELIEF®

FIRST AID
SHOT THERAPY®

WARMING PEACH

FDA
COMPLIANT

Diphenhydramine HCl
Nighttime sleep-aid
Alcohol 10%

1.35 FL OZ (40mL)